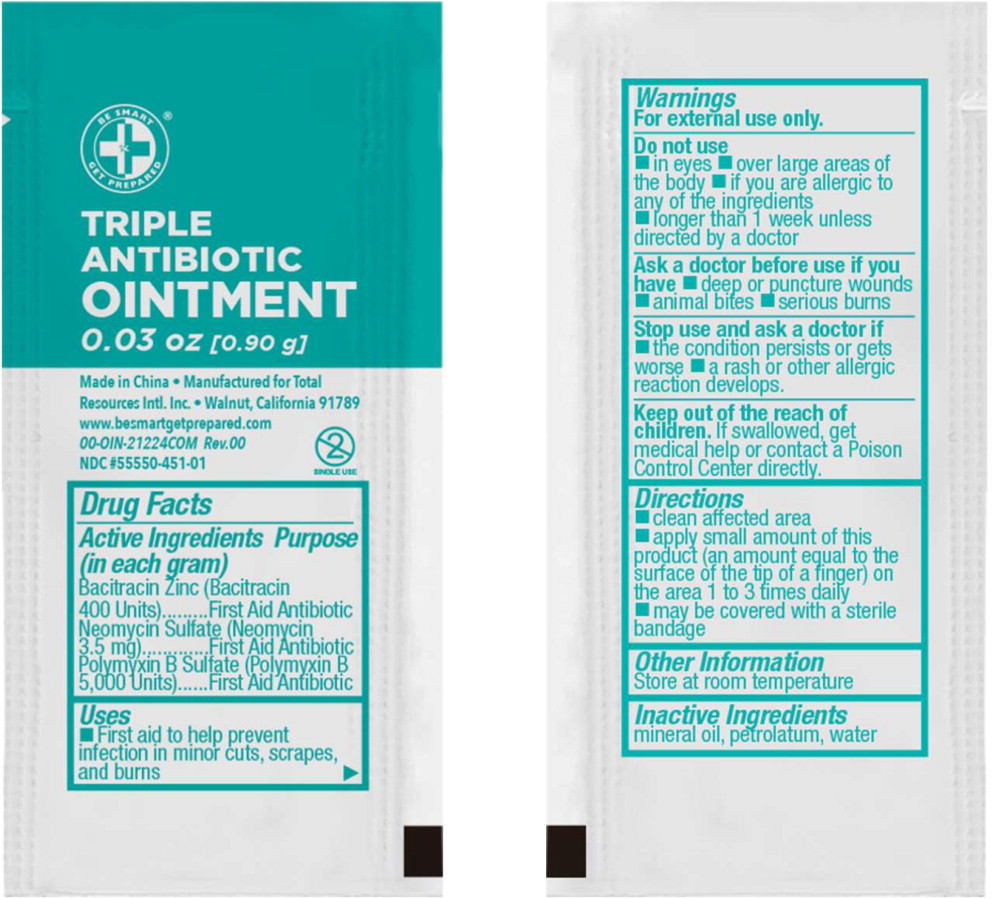 DRUG LABEL: Be Smart Get Prepared Triple Antibiotic
NDC: 55550-451 | Form: OINTMENT
Manufacturer: Total Resources International, Inc
Category: otc | Type: HUMAN OTC DRUG LABEL
Date: 20240816

ACTIVE INGREDIENTS: BACITRACIN ZINC 400 [USP'U]/1 g; NEOMYCIN SULFATE 0.0035 g/1 g; POLYMYXIN B SULFATE 5000 [USP'U]/1 g
INACTIVE INGREDIENTS: MINERAL OIL; WHITE PETROLATUM; WATER

Drug Facts

Active Ingredients (in each gram)

Bacitracin Zinc (Bacitracin 400 Units)

Neomycin Sulfate (Neomycin 3.5mg)

Polymyxin B Sulfate (Polymyxin B 5,000 Units)

Purpose

First Aid Antibiotic

First Aid Antibiotic

First Aid Antibiotic

Uses

- First aid to help prevent infection in minor cuts, scrapes, and burns

Warnings

For external use only.

Do not use

- in eyes
- over large areas of the body
- if you are allergic to any of the ingredients
- longer than 1 week unless directed by a doctor

Ask a doctor if before use if you have

- deep or puncture wounds
- animal bites
- serious burns

Stop use and ask a doctor if

- the condition persists or gets worse
- a rash or other allergic reaction develops

Keep out of reach of children. If swallowed, get medical help or contact a Poison Control Center directly.

Directions

- clean affected area
- apply small amount of this product (an amount equal to the surface of the tip of a finger) on the area 1 to 3 times daily
- may be covered with a sterile bandage

Other Information

Store at room temperature

Inactive Ingredients

mineral oil, petrolatum, water

Principal Display Panel – 0.90mL Pouch Label

BE SMART

GET PREPARED®

TRIPLE ANTIBIOTIC OINTMENT

0.03 oz [0.90 g]

Single Use

Made in China

Manufactured for Total Resources Intl. Inc.

Walnut, California 91789

www.besmartgetprepared.com • 00-OIN-21224COM Rev. 00

NDC 55550-451-01